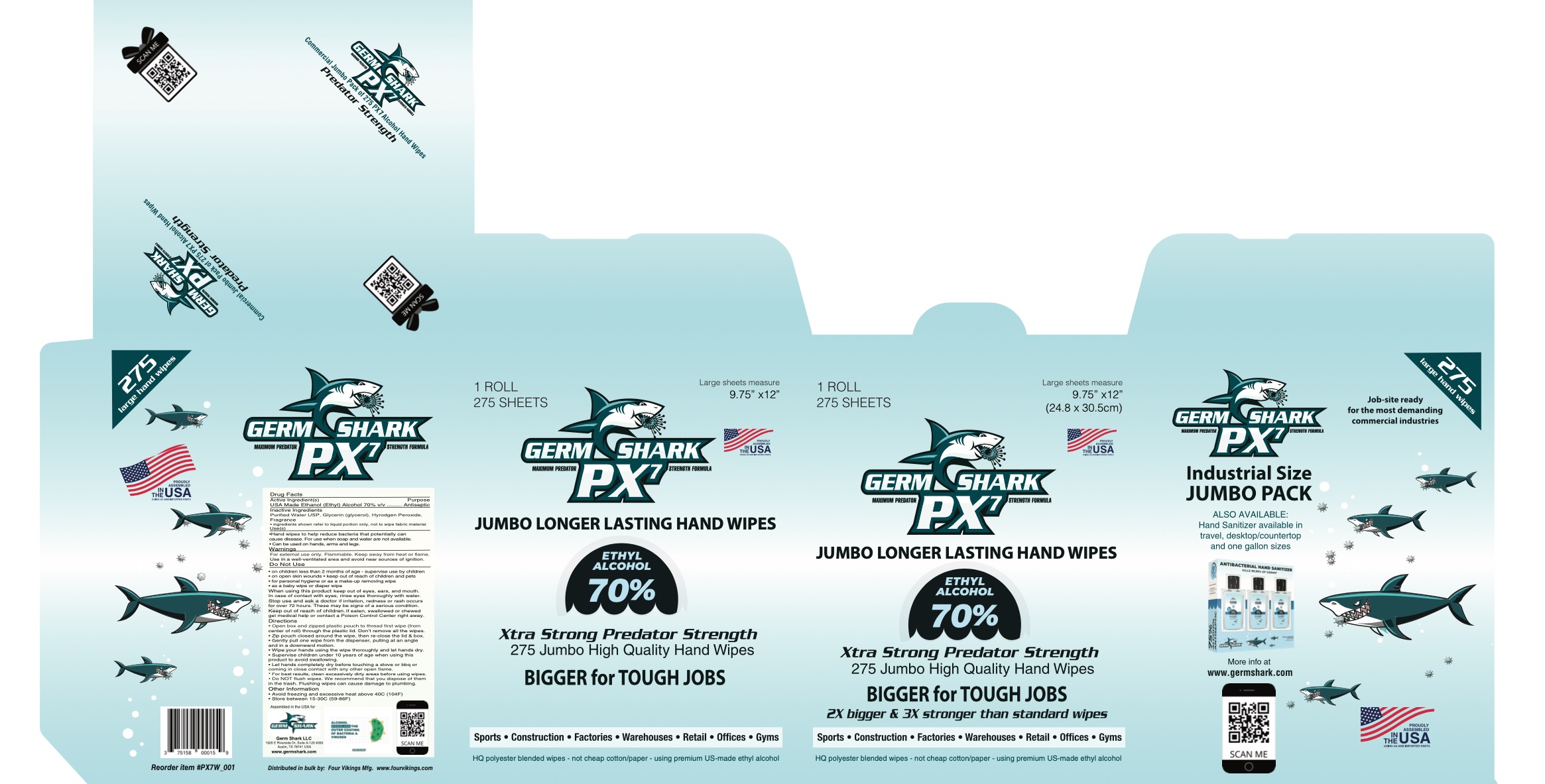 DRUG LABEL: Germ Shark PX7 Hand Jumbo Hand Sanitizing Wipes
NDC: 75158-004 | Form: CLOTH
Manufacturer: Germ Shark LLC
Category: otc | Type: HUMAN OTC DRUG LABEL
Date: 20200917

ACTIVE INGREDIENTS: ALCOHOL 0.7 mL/1 mL
INACTIVE INGREDIENTS: WATER; GLYCERIN; HYDROGEN PEROXIDE

Germ Shark PX7 Hand Jumbo Hand Sanitizing Wipes

Active Ingredient(s)

USA Made Ethanol (Ethyl) Alcohol 70% v/v

Purpose

Antiseptic

Inactive Ingredients

Purified Water USP, Glycerin (glycerol), Hyrodgen Peroxide, Fragrance

*ingredients shown refer to liquid portion only, not to wipe fabric material

Use(s)

*Hand wipes to help reduce bacteria that potentially can cause disease. For use when soap and water are not available.

Can be used on hands, arms and legs.

Warnings

For external use only. Flammable. Keep away from heat or flame.

Use in a well-ventillated area and avoid near sources of ignition.

Do Not Use

- on children less than 2 months of age - supervise use by children
- on open skin wounds
- keep out of reach of children and pets
- for personal hygiene or as a make-up removing wipes
- as a baby wipe or diaper wipe

When using this product

keep out of eyes, ears, and mouth. In case of contact with eyes, rinse eyes thoroughly with water.

Stop use and ask a doctor

if irritation, redness or rash occurs for over 72 hours. These may be signs of a serious condition.

Keep out of reach of children.

If eaten, swallowed or chewed get medical help or contact a Poison Control Center right away.

Directions

- Open box and zipped plastic pouch to thread first wipe (from center of roll) through the plastic lid. Don't remove all the wipes.
- Zip pouch closed around the wipe. then re-close the lid & box.
- Gently pull one wipe from the dispenser, pulling at an angle and in a downward motion.
- Wipe your hands using the wipe thoroughly and let hands dry.
- Supervise children under 10 years of age when using this product to avoid swallowing.
- Let hands completely dry before touching a stove or bbq or coming in close contact with any other open flame.
- For best results, clean excessively dirty areas before using wipes.
- Do Not flush wipes. We recommend that you dispose of them in the trash. Flushing wipes can cause damage to plumbing.

Other Information

• Avoid freezing and excessive heat above 40C (104F)
• Store between 15-30C (59-86F)